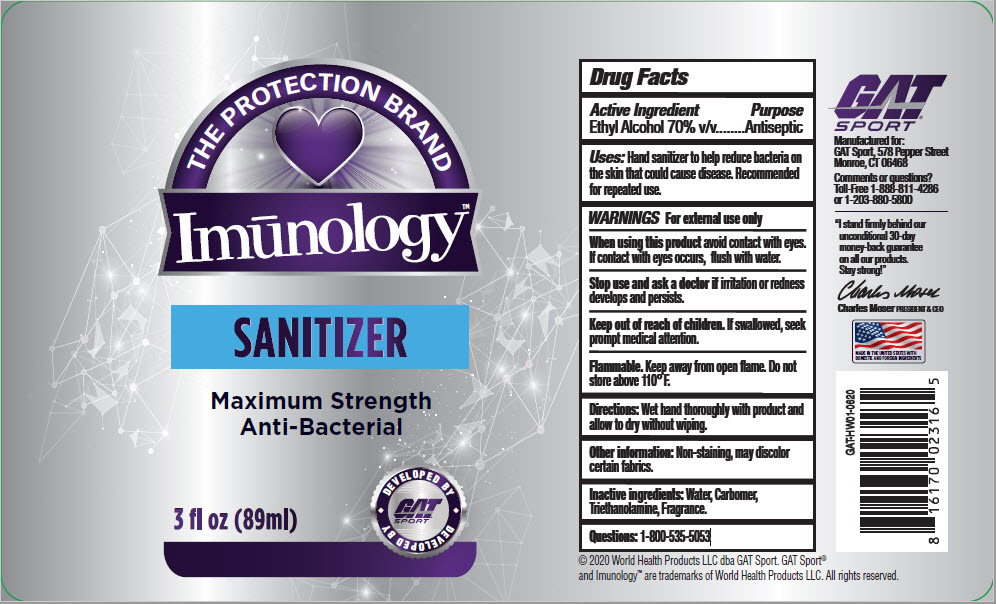 DRUG LABEL: Imunology Sanitizer
NDC: 79636-003 | Form: LIQUID
Manufacturer: World Health Products, LLC
Category: otc | Type: HUMAN OTC DRUG LABEL
Date: 20200727

ACTIVE INGREDIENTS: Alcohol 70 mg/100 mL
INACTIVE INGREDIENTS: Water; Carbomer Homopolymer, Unspecified Type; Trolamine

Imūnology™ Sanitizer

Drug Facts

Active Ingredient

Ethyl Alcohol 70% v/v

Purpose

Antiseptic

Uses

Hand sanitizer to help reduce bacteria on the skin that could cause disease. Recommended for repeated use.

WARNINGS

For external use only

When using this product avoid contact with eyes. If contact with eyes occurs, flush with water.

Stop use and ask a doctor if irritation or redness develops and persists.

Keep out of reach of children. If swallowed, seek prompt medical attention.

STORAGE AND HANDLING

Flammable. Keep away from open flame. Do not store above 110° F.

Directions

Wet hand thoroughly with product and allow to dry without wiping.

Other information

Non-staining, may discolor certain fabrics.

Inactive ingredients

Water, Carbomer, Triethanolamine, Fragrance.

Questions

1-800-535-5053

PRINCIPAL DISPLAY PANEL - 89 ml Bottle Label

THE PROTECTION BRAND

Imūnology™

SANITIZER

Maximum Strength
Anti-Bacterial

3 fl oz (89ml)

DEVELOPED BY
GAT®
SPORT
DEVELOPED BY